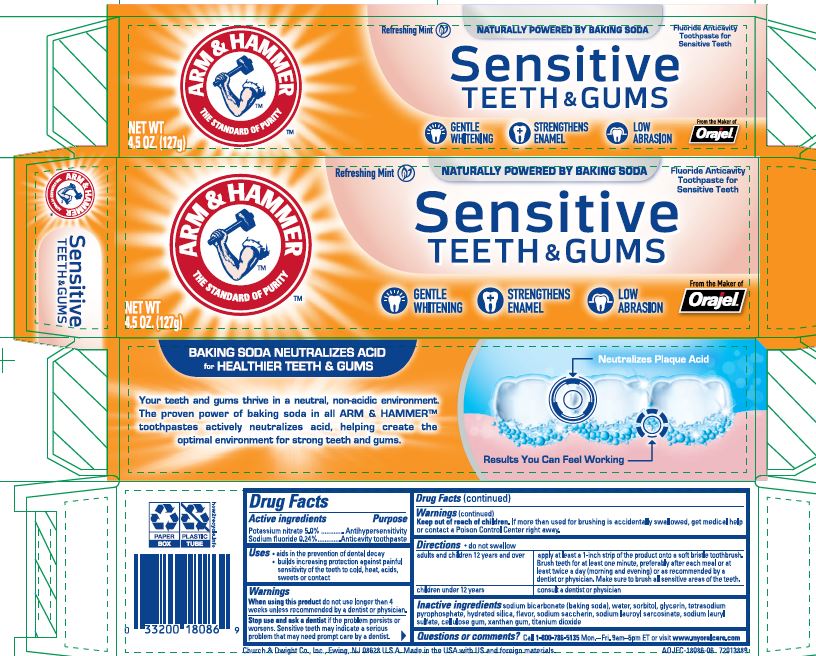 DRUG LABEL: Sensitive Teeth and Gums
NDC: 10237-669 | Form: PASTE, DENTIFRICE
Manufacturer: Church & Dwight Co., Inc.
Category: otc | Type: HUMAN OTC DRUG LABEL
Date: 20251212

ACTIVE INGREDIENTS: SODIUM FLUORIDE 2.43 mg/1 g; POTASSIUM NITRATE 50 mg/1 g
INACTIVE INGREDIENTS: SODIUM BICARBONATE; WATER; SORBITOL; GLYCERIN; HYDRATED SILICA; SACCHARIN; SODIUM LAURYL SULFATE; SODIUM LAUROYL SARCOSINATE; CARBOXYMETHYLCELLULOSE SODIUM, UNSPECIFIED; TITANIUM DIOXIDE; XANTHAN GUM; SODIUM PYROPHOSPHATE

Arm and Hammer Sensitive Teeth and Gums

Active ingredients
Potassium nitrate 5.0%
Sodium fluoride 0.24%

Purpose

Antihypersensitivity

Anticavity toothpaste

Use

- aids in the prevention of dental decay
- builds increasing protection against painful sensitivity of the teeth to cold, heat, acids, sweets or contact

Warnings
When using this product do not use longer than 4 weeks unless recommended by a dentist or physician.

Stop use and ask a dentistif the problem persists or worsens. Sensitive teeth may indicate a serious problem that may need prompt care by a dentist.

Keep out of reach of children under 6 years of age.
If more than used for brushing is accidentally swallowed, get medical help or contact a Poison Control Center right away.

DOSAGE AND ADMINISTRATION

Directions do not swallow

adults and children 12 years and older

- apply at least a 1-inch strip of the product onto a soft bristly toothbrush. Brush teeth for at least one minute, preferable after each meal or at least twice a day (morning and evening) or as recommended by a dentist or physician. Make sure to brush all sensitive areas of the teeth.

children under 12 years

- consult a dentist or physician

INACTIVE INGREDIENT

Inactive ingredients sodium bicarbonate (baking soda), water, sorbitol, glycerin, hydrated silica, flavor, sodium saccharin, sodium lauroyl sarcosinate, sodium lauryl sulfate, cellulose gum, titanium dioxide, xanthan gum

Questions or comments? Call 1-800-786-5135Monday-Friday 9am-5pm ET or visit www.myoralcare.com

Principal Display Panel

ARM AND HAMMER The Standard of Purity

Refreshing Mint Naturally Powered By Baking Soda Fluoride Anticavity Toothpaste for Sensitive Teeth

Sensitive Teeth and Gums

NET WT.

4.5 OZ. (127g) Gentle Whitening Strengthens Enamel Low Abrasion From the Maker of Orajel